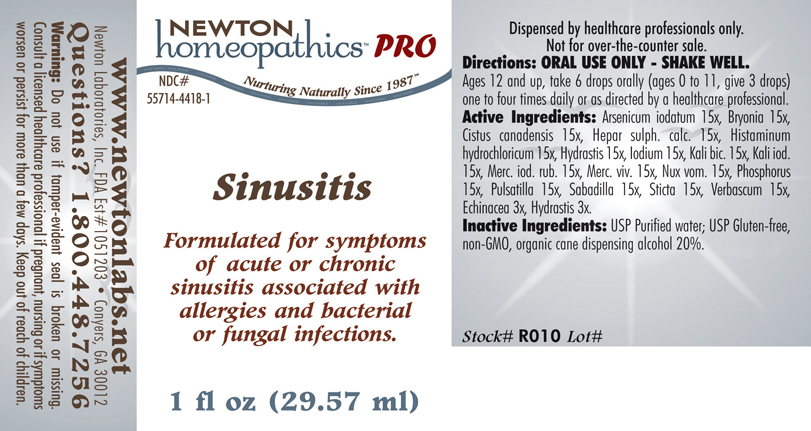 DRUG LABEL: Sinusitis 
NDC: 55714-4418 | Form: LIQUID
Manufacturer: Newton Laboratories, Inc.
Category: homeopathic | Type: HUMAN PRESCRIPTION DRUG LABEL
Date: 20110601

ACTIVE INGREDIENTS: Arsenic Triiodide 15 [hp_X]/1 mL; Bryonia Alba Root 15 [hp_X]/1 mL; Helianthemum Canadense 15 [hp_X]/1 mL; Calcium Sulfide 15 [hp_X]/1 mL; Histamine Dihydrochloride 15 [hp_X]/1 mL; Goldenseal 15 [hp_X]/1 mL; Iodine 15 [hp_X]/1 mL; Potassium Dichromate 15 [hp_X]/1 mL; Potassium Iodide 15 [hp_X]/1 mL; Mercuric Iodide 15 [hp_X]/1 mL; Mercury 15 [hp_X]/1 mL; Strychnos Nux-vomica Seed 15 [hp_X]/1 mL; Phosphorus 15 [hp_X]/1 mL; Pulsatilla Vulgaris 15 [hp_X]/1 mL; Schoenocaulon Officinale Seed 15 [hp_X]/1 mL; Lobaria Pulmonaria 15 [hp_X]/1 mL; Verbascum Thapsus 15 [hp_X]/1 mL; Echinacea, Unspecified 3 [hp_X]/1 mL; Goldenseal 3 [hp_X]/1 mL
INACTIVE INGREDIENTS: Alcohol

Sinusitis

PRODUCT NAME & INDICATIONS SECTION

Sinusitis Formulated for symptoms of acute or chronic sinusitis associated with allergies and bacterial or fungal infections.

DIRECTION SECTION

Directions: ORAL USE ONLY - SHAKE WELL. Ages 12 and up, take 6 drops orally (ages 0 to 11, give 3 drops) one to four times daily or as directed by a healthcare professional.

ACTIVE INGREDIENT SECTION

Arsenicum iodatum 15x, Bryonia 15x, Cistus canadensis 15x, Hepar sulph. calc. 15x, Histaminum hydrochloricum 15x, Hydrastis 15x, Iodium 15x, Kali bic. 15x, Kali iod.15x, Merc. iod. rub. 15x, Merc. viv. 15x, Nux vom. 15x, Phosphorus 15x, Pulsatilla 15x, Sabadilla 15x, Sticta 15x, Verbascum 15x , Echinacea 3x, Hydrastis 3x.

PURPOSE SECTION

Formulated for symptoms of acute or chronic sinusitis associated with allergies and bacterial or fungal infections.

INACTIVE INGREDIENT SECTION

Inactive Ingredients: USP Purified Water; USP Gluten-free, non-GMO, organic cane dispensing alcohol 20%.

QUESTIONS? SECTION

www.newtonlabs.net Newton Laboratories, Inc. FDA Est # 1051203 - Conyers, GA 30012
Questions? 1.800.448.7256

WARNINGS SECTION

Warning: Do not use if tamper - evident seal is broken or missing. Consult a licensed healthcare professional if pregnant, nursing or if symptoms worsen or persist for more than a few days. Keep out of reach of children.

OTC - PREGNANCY OR BREAST FEEDING SECTION

Consult a licensed healthcare professional if pregnant, nursing or if symptoms worsen or persist for more than a few days

OTC - KEEP OUT OF REACH OF CHILDREN SECTION

Keep out of reach of children.